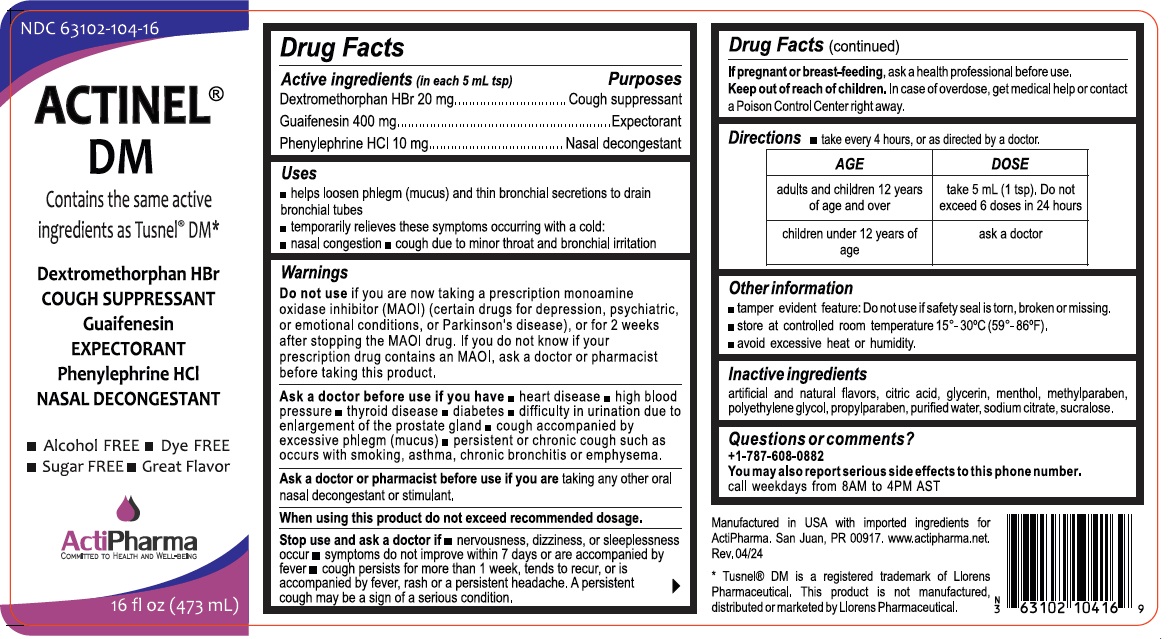 DRUG LABEL: ACTINEL DM
NDC: 63102-104 | Form: SOLUTION
Manufacturer: ACTIPHARMA, LLC
Category: otc | Type: HUMAN OTC DRUG LABEL
Date: 20240628

ACTIVE INGREDIENTS: DEXTROMETHORPHAN HYDROBROMIDE 20 mg/5 mL; GUAIFENESIN 400 mg/5 mL; PHENYLEPHRINE HYDROCHLORIDE 10 mg/5 mL
INACTIVE INGREDIENTS: CITRIC ACID MONOHYDRATE; GLYCERIN; MENTHOL, UNSPECIFIED FORM; METHYLPARABEN; POLYETHYLENE GLYCOL 400; PROPYLPARABEN; WATER; SODIUM CITRATE, UNSPECIFIED FORM; SUCRALOSE

ACTINEL® DM

Active ingredients (in each 5 mL tsp)

Dextromethorphan HBr 20 mg
Guaifenesin 400 mg
Phenylephrine HCl 10 mg

Purposes

Cough suppressant
Expectorant
Nasal decongestant

Uses

• helps loosen phlegm (mucus) and thin bronchial secretions to drain bronchial tubes
• temporarily relieves these symptoms occurring with a cold:
• nasal congestion • cough due to minor throat and bronchial irritation

Warnings

Do not use if you are now taking a prescription monoamine oxidase inhibitor (MAOI) (certain drugs for depression, psychiatric, or emotional conditions, or Parkinson's disease), or for 2 weeks after stopping the MAOI drug. If you do not know if your prescription drug contains an MAOI, ask a doctor or pharmacist before taking this product.

Ask a doctor before use if you have • heart disease • high blood pressure • thyroid disease • diabetes • difficulty in urination due to enlargement of the prostate gland • cough accompanied by excessive phlegm (mucus) • persistent or chronic cough such as occurs with smoking, asthma, chronic bronchitis or emphysema.

Ask a doctor or pharmacist before use if you are taking any other oral nasal decongestant or stimulant.

When using this product do not exceed recommended dosage.

Stop use and ask a doctor if • nervousness, dizziness, or sleeplessness occur • symptoms do not improve within 7 days or are accompanied by fever • cough persists for more than 1 week, tends to recur, or is accompanied by fever, rash or a persistent headache. A persistent cough may be a sign of a serious condition.

If pregnant or breast-feeding, ask a health professional before use.

Keep out of reach of children. In case of overdose, get medical help or contact a Poison Control Center right away.

Directions

- take every 4 hours, or as directed by a doctor.

AGE | DOSE
adults and children 12 years; of age and over | take 5mL (1tsp). Do not; exceed 6 doses in 24 hours
Children under 12 years of age | ask a doctor

Other information

• tamper evident feature: Do not use if safety seal is torn, broken or missing.
• store at controlled room temperature 15°- 30°C (59°- 86°F).
• avoid excessive heat or humidity.

Inactive ingredients

artificial and natural flavors, citric acid, glycerin, menthol, methylparaben, polyethylene glycol, propylparaben, purified water, sodium citrate, sucralose.

Questions or comments?

+1-787-608-0882
You may also report serious side effects to this phone number.
call weekdays from 8AM to 4PM AST

Contains the same active ingredients as Tusnel® DM*

• Alcohol FREE • Dye FREE

• Sugar FREE • Great Flavor

Manufactured in USA with imported ingredients for ActiPharma. San Juan, PR 00917. www.actipharma.net.

* Tusnel® DM is a registered trademark of Llorens Pharmaceutical. This product is not manufactured, distributed or marketed by Llorens Pharmaceutical.